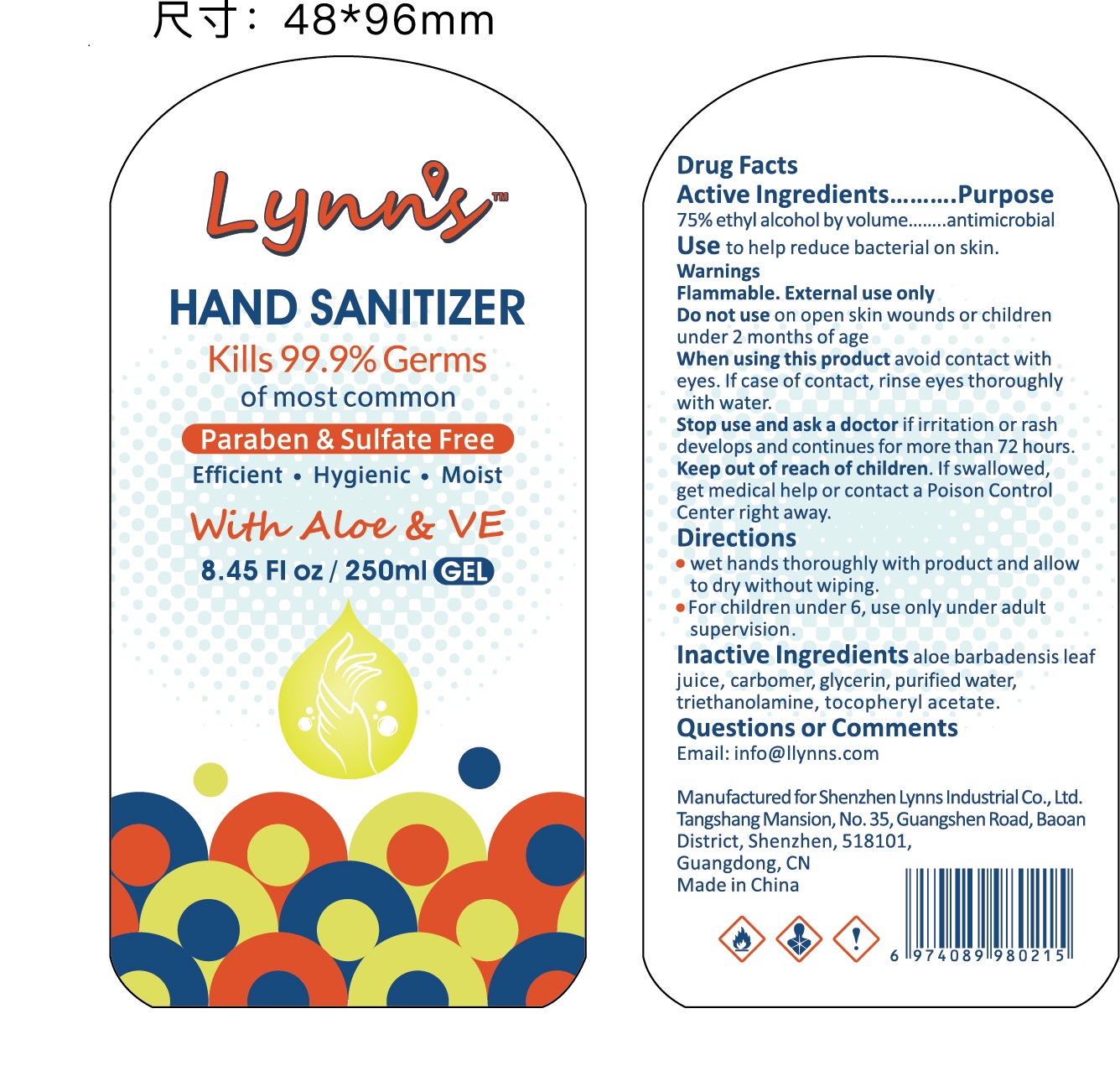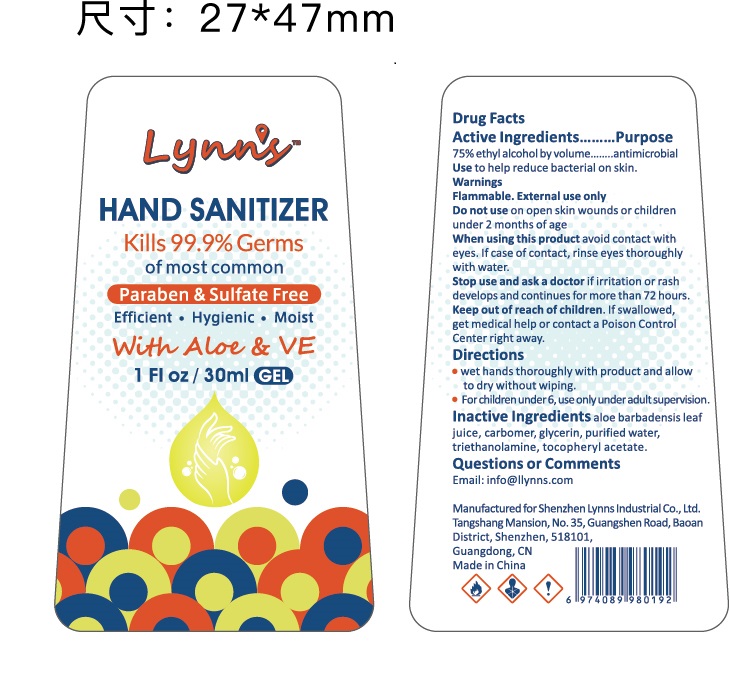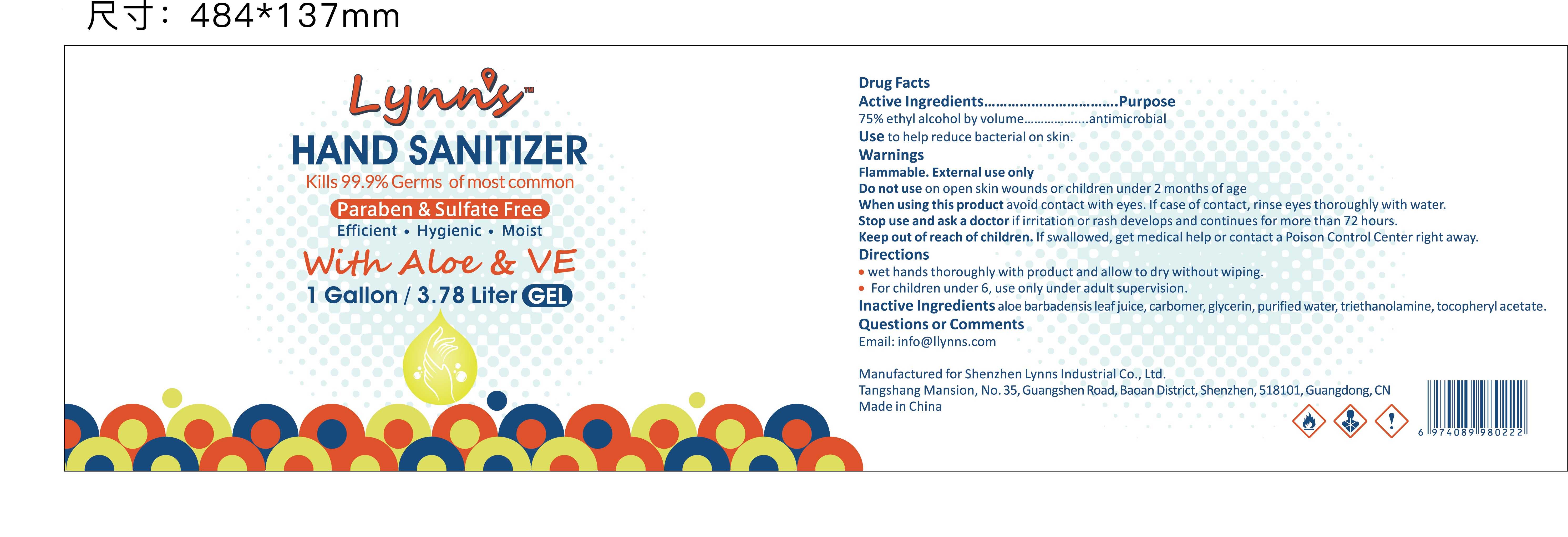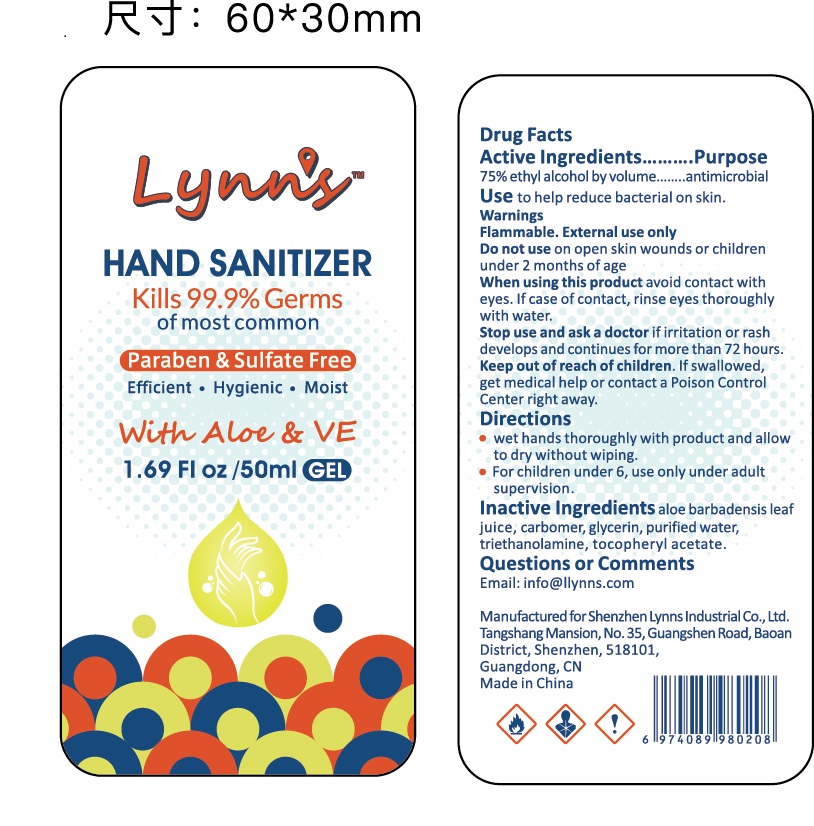 DRUG LABEL: Hand Sanitizer
NDC: 81422-008 | Form: GEL
Manufacturer: Shenzhen Lynns Industrial Co., Ltd.
Category: otc | Type: HUMAN OTC DRUG LABEL
Date: 20210118

ACTIVE INGREDIENTS: ALCOHOL 75 mL/100 mL
INACTIVE INGREDIENTS: GLYCERIN; ALOE VERA LEAF; WATER; TROLAMINE; ALPHA-TOCOPHEROL ACETATE; CARBOMER HOMOPOLYMER, UNSPECIFIED TYPE

81422-008
Hand Sanitizer Gel

Active Ingredient(s)

75%ethyl alcohol by volume....antimicrobial

Purpose

antimicrobial

Use

Use to help reduce bacterial on skin.

Warnings

Flammable.External use only

Do not use on open skin wounds or children under 2 months of age

When using this product avoid contact with eyes.If case of contact, rinse eyes thoroughly with water.

Stop use and ask a doctor if irritation or rash develops and continues for more than 72 hours.

Keep out of reach of children.If swallowed, get medical help or contact a Poison Control Center right away.

Do not use on open skin wounds or children under 2 months of age

When using this product avoid contact with eyes.If case of contact, rinse eyes thoroughly with water.

Stop use and ask a doctor if irritation or rash develops and continues for more than 72 hours.

Keep out of reach of children.If swallowed, get medical help or contact a Poison Control Center right away.

Stop use and ask a doctor if irritation or rash develops and continues for more than 72 hours.

Keep out of reach of children.If swallowed, get medical help or contact a Poison Control Center right away.

Directions

·wet hands thoroughly with product and allow to dry without wiping.
·For children under 6, use only under adult supervision.

Other information

- Store between 15-30C (59-86F)
- Avoid freezing and excessive heat above 40C (104F)

Inactive ingredients

aloe barbadensis leaf juice, carbomer, glycerin, purified water, triethanolamine, tocopheryl acetate.

Package Label - Principal Display Panel

81422-008-25--Hand Sanitizer Gel 250ml

81422-008-30--Hand Sanitizer Gel 30ml

81422-008-37--Hand Sanitizer Gel 1 Gallon

81422-008-50--Hand Sanitizer Gel 50ml